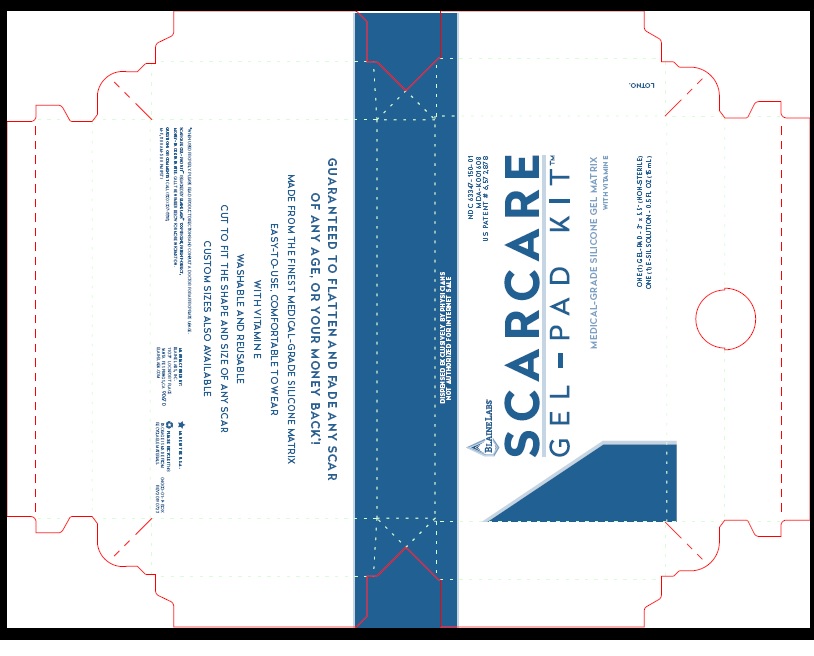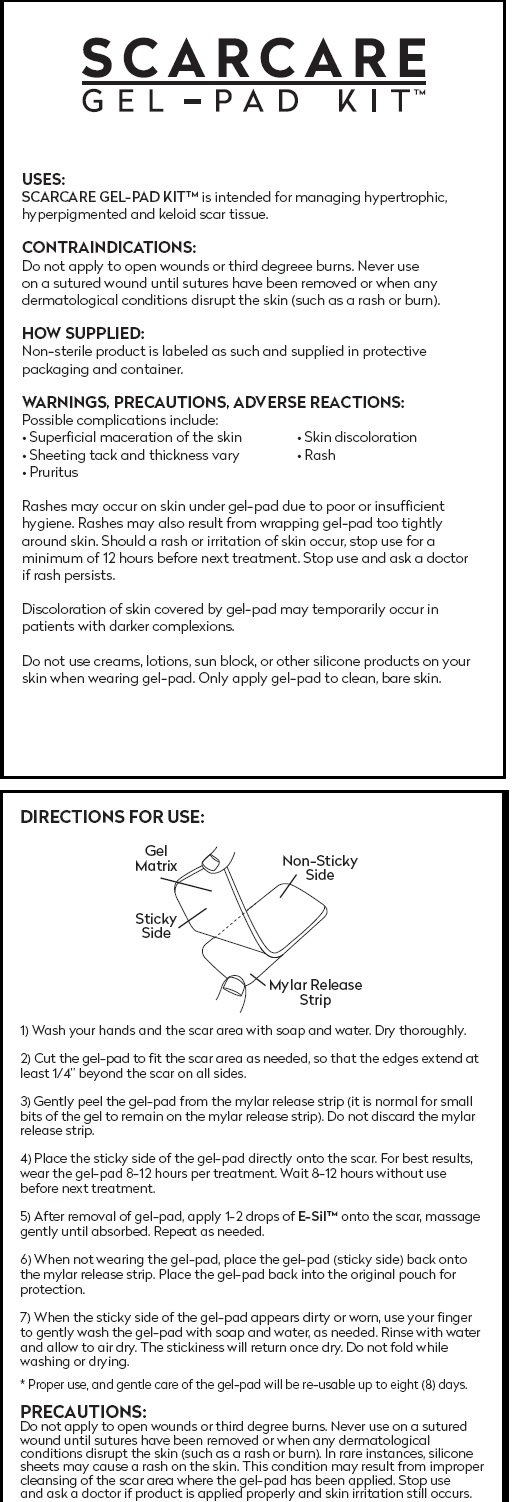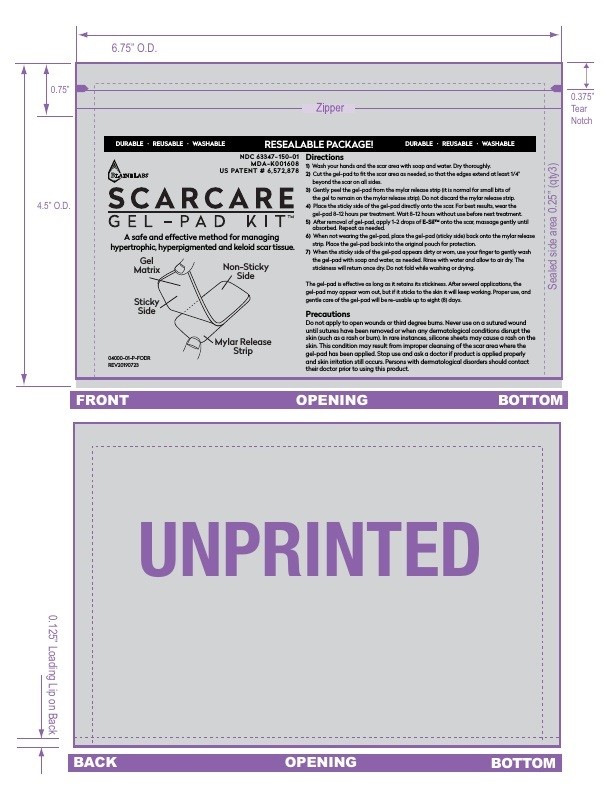 DRUG LABEL: SCARCARE GEL-PAD KIT
NDC: 63347-150
Manufacturer: Blaine Labs Inc.
Category: other | Type: MEDICAL DEVICE
Date: 20190730

SCARCARE GEL-PAD KIT

USES:
SCARCARE GEL-PAD KIT™ is intended for managing hypertrophic, hyperpigmented and keloid scar tissue.

CONTRAINDICATIONS:
Do not apply to open wounds or third degreee burns. Never use on a sutured wound until sutures have been removed or when any dermatological conditions disrupt the skin (such as a rash or burn).

HOW SUPPLIED:
Non-sterile product is labeled as such and supplied in protective packaging and container.

WARNINGS, PRECAUTIONS, ADVERSE REACTIONS:
Possible complications include:
• Superficial maceration of the skin • Skin discoloration
• Sheeting tack and thickness vary • Rash
• Pruritus

Rashes may occur on skin under gel-pad due to poor or insufficient
hygiene. Rashes may also result from wrapping gel-pad too tightly
around skin. Should a rash or irritation of skin occur, stop use for a
minimum of 12 hours before next treatment. Stop use and ask a doctor
if rash persists.

Discoloration of skin covered by gel-pad may temporarily occur in
patients with darker complexions.

Do not use creams, lotions, sun block, or other silicone products on your
skin when wearing gel-pad. Only apply gel-pad to clean, bare skin.

INDICATIONS AND USAGE

DIRECTIONS FOR USE:
1) Wash your hands and the scar area with soap and water. Dry thoroughly.

2) Cut the gel-pad to fit the scar area as needed, so that the edges extend at least 1/4” beyond the scar on all sides.

3) Gently peel the gel-pad from the mylar release strip (it is normal for small bits of the gel to remain on the mylar release strip). Do not discard the mylar release strip.

4) Place the sticky side of the gel-pad directly onto the scar. For best results, wear the gel-pad 8-12 hours per treatment. Wait 8-12 hours without use before next treatment.

5) After removal of gel-pad, apply 1-2 drops of E-Sil™ onto the scar, massage gently until absorbed. Repeat as needed.

6) When not wearing the gel-pad, place the gel-pad (sticky side) back onto the mylar release strip. Place the gel-pad back into the original pouch for protection.

7) When the sticky side of the gel-pad appears dirty or worn, use your finger to gently wash the gel-pad with soap and water, as needed. Rinse with water and allow to air dry. The stickiness will return once dry. Do not fold while washing or drying.

* Proper use, and gentle care of the gel-pad will be re-usable up to eight (8) days.

PRECAUTIONS:
Do not apply to open wounds or third degree burns. Never use on a sutured wound until sutures have been removed or when any dermatological conditions disrupt the skin (such as a rash or burn). In rare instances, silicone sheets may cause a rash on the skin. This condition may result from improper cleansing of the scar area where the gel-pad has been applied. Stop use and ask a doctor if product is applied properly and skin irritation still occurs. Persons with dermatological disorders should contact their doctor prior to using this product.

Product Label

BLAINELABS

NDC 63347- 150-01
MDA-K001608
US PATENT # 6,572,878

SCARCARE

GEL-PAD MATRIX

MEDICAL-GRADE SILICONE GEL MATRIX
WITH VITAMIN E

ONE (1) GEL-PAD - 3” x 5.5” (NON-STERILE)
ONE (1) E-SIL SOLUTION - 0.5 FL OZ (15 mL)

GUARANTEED TO FLATTEN AND FADE ANY SCAR
OF ANY AGE, OR YOUR MONEY BACK*!

MADE FROM THE FINEST MEDICAL-GRADE SILICONE MATRIX

EASY-TO-USE, COMFORTABLE TO WEAR
WITH VITAMIN E

WASHABLE AND REUSABLE

CUT TO FIT THE SHAPE AND SIZE OF ANY SCAR

CUSTOM SIZES ALSO AVAILABLE

*WHEN USED PROPERLY. PLEASE READ PRODUCT DIRECTIONS AND CONSULT A DOCTOR FOR APPROPRIATE USAGE.

SCARCARE GEL-PAD KIT™ IS BACKED BY BLAINE LABS®’ 100 PERCENT, PATIENT-DIRECT,

MONEY-BACK GUARANTEE. CALL THE NUMBER BELOW FOR MORE INFORMATION.

QUESTIONS OR COMMENTS? CALL (800) 307-8818,

M-F, 8:00 AM-5:00 PM (PST)

MANUFACTURED BY:
BLAINE LABS, INC.
1 1 0 3 7 LOCKPORT PLACE
SANTA FE SPRINGS, CA 90670
BLAINELABS.COM

MADE IN THE U.S.A.

PLEASE RECYCLE! THIS
PACKAGE IS MADE FROM
RECYCLABLE MATERIALS.

04000-01-P-BOX
REV20190723

DISPENSED EXCLUSIVELY BY PHYSICIANS
NOT AUTHORIZED FOR INTERNET SALE

------------------------------------------------------

Outer Box

Inner Foil

Insert

rege